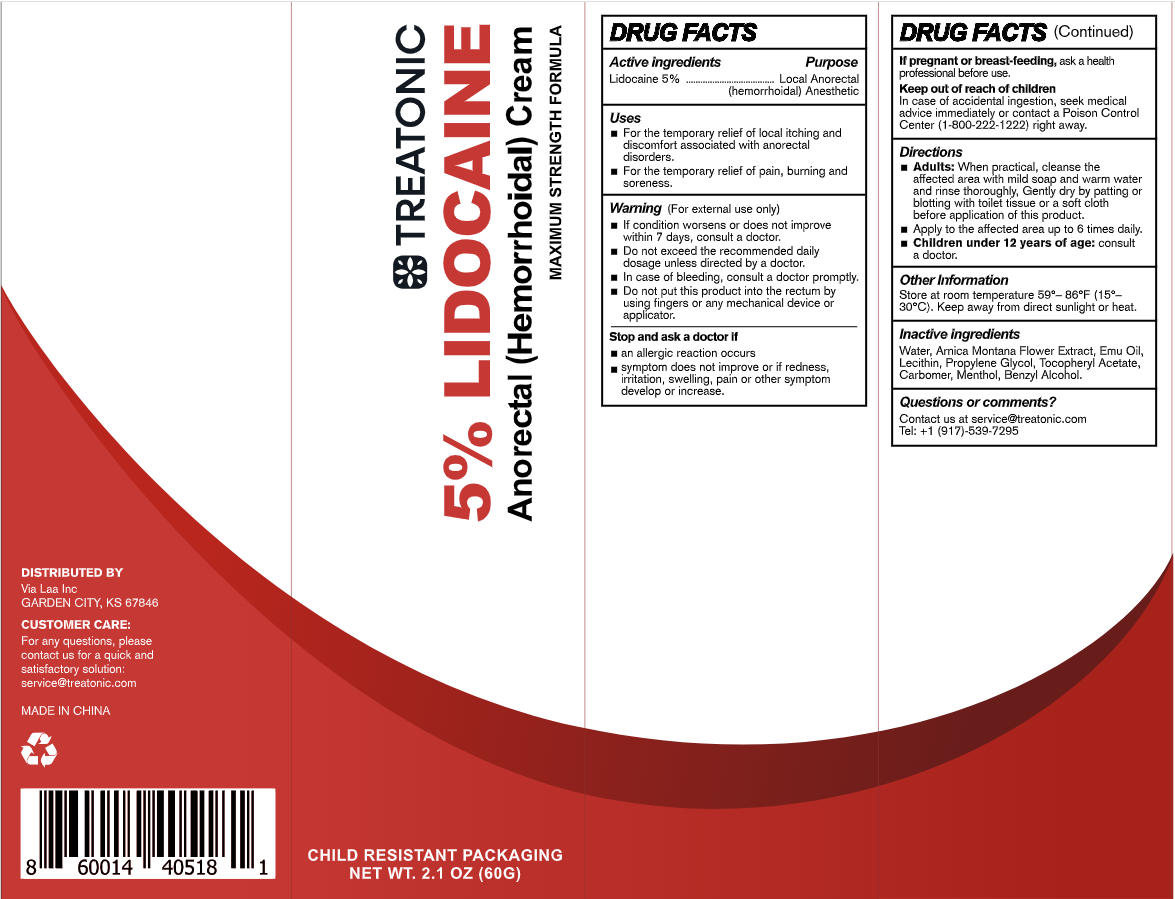 DRUG LABEL: Treatonic 5% Lidocaine Cream
NDC: 85569-014 | Form: CREAM
Manufacturer: 100 KARMA INC
Category: otc | Type: HUMAN OTC DRUG LABEL
Date: 20260203

ACTIVE INGREDIENTS: LIDOCAINE 3 g/60 g
INACTIVE INGREDIENTS: PROPYLENE GLYCOL; LECITHIN, SOYBEAN; MENTHOL; EMU OIL; WATER; BENZYL ALCOHOL; CARBOMER; ARNICA MONTANA FLOWER WATER; ALPHA-TOCOPHEROL ACETATE

85569-014- Initial Treatonic 5% Lidocaine Cream

ACTIVE INGREDIENT

Lidocaine 5%

PURPOSE

Local Anorectal

(hemorrhoidal) Anesthetic

DOSAGE AND ADMINISTRATION

For the temporary relief of local itching and discomfort associated withe anorectal disorders.

For the temporary relief of pain, burning and soreness.

WARNINGS

For external use only

WHEN USING

- IF condition worsens or does not improve within 7 days, consult a doctor.
- Do not exceed the recommended daily dosage unless directed by a doctor.
- In case of bleeding, consult a doctor promptly.
- Do no t put this product into the rectum by using fingers or any mechanical device or applicatior.

ASK DOCTOR/PHARMACIST

- An allergic reaction occurs
- Symptom does not improve or if redness, irritation, swelling, pain or other symptom develop or increase.

PREGNANCY OR BREAST FEEDING

Ask a health professional before use.

KEEP OUT OF REACH OF CHILDREN

In case of accidental ingestion, seek medical advice immediately or contact a Poison Control Center (1-800-222-1222) right away.

INDICATIONS AND USAGE

- Adults: When practical, cleanse the affected area with mild soap and warm water and rinse thoroughly, Gently dry by patting o rblotting with toilet tissue or a soft clothbefore application of this product.
- Apply to the affected area up to 6 times daily.
- Chlldren under 12 years of age: consulta doctor.

OTHER SAFETY INFORMATION

Store at room temperature 59°- 86°F (15°-30°C). Keep away from direct sunlight or heat.

INACTIVE INGREDIENT

Water, Arnica Montana Flower Extract, Emu Oil,Lecithin, Propylene Glycol, Tocopheryl Acetate,Carbomer, Menthol, Benzyl Alcohol.

QUESTIONS

Contact us at service@treatonic.com

Tel: +1 (917)-539-7295